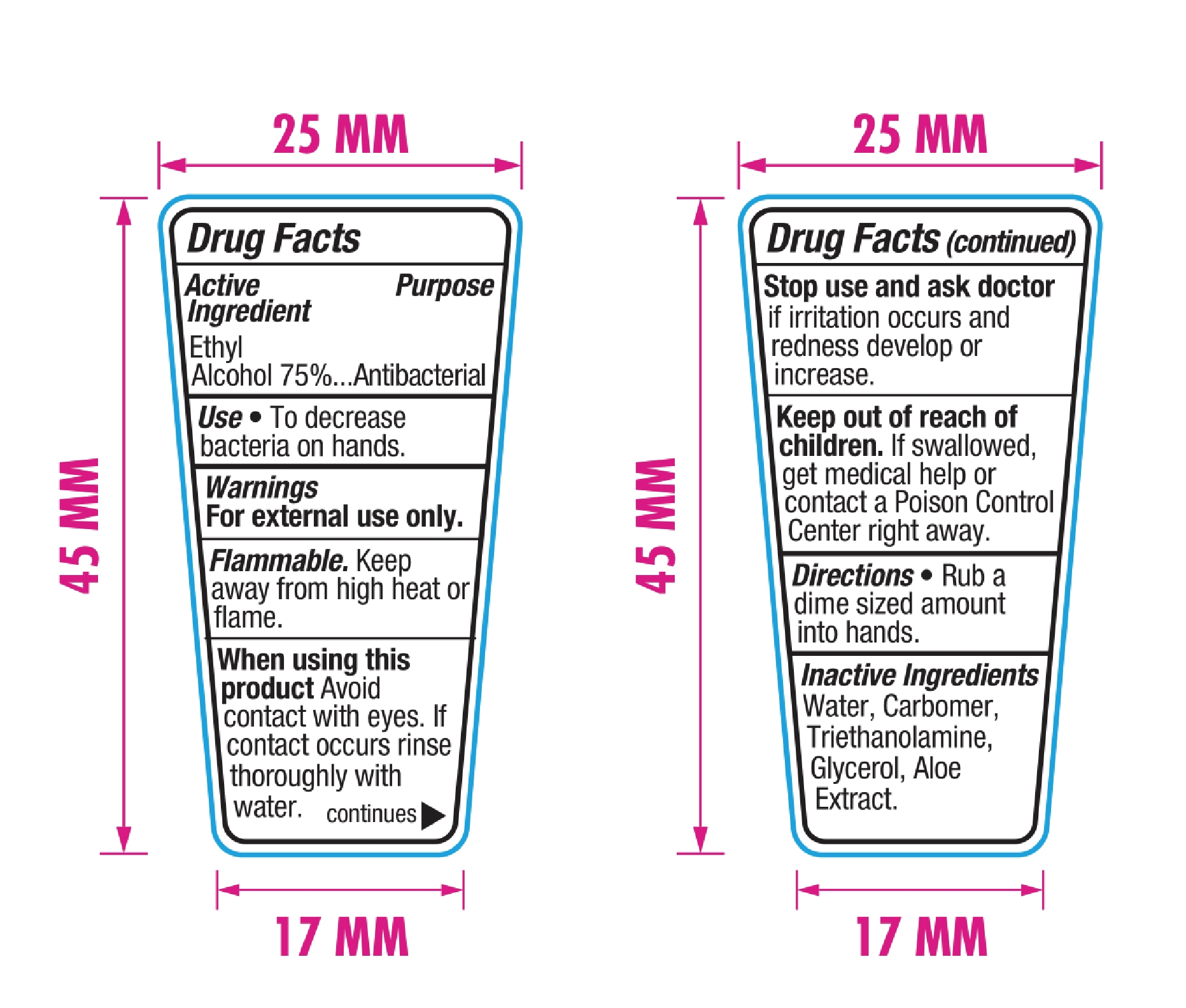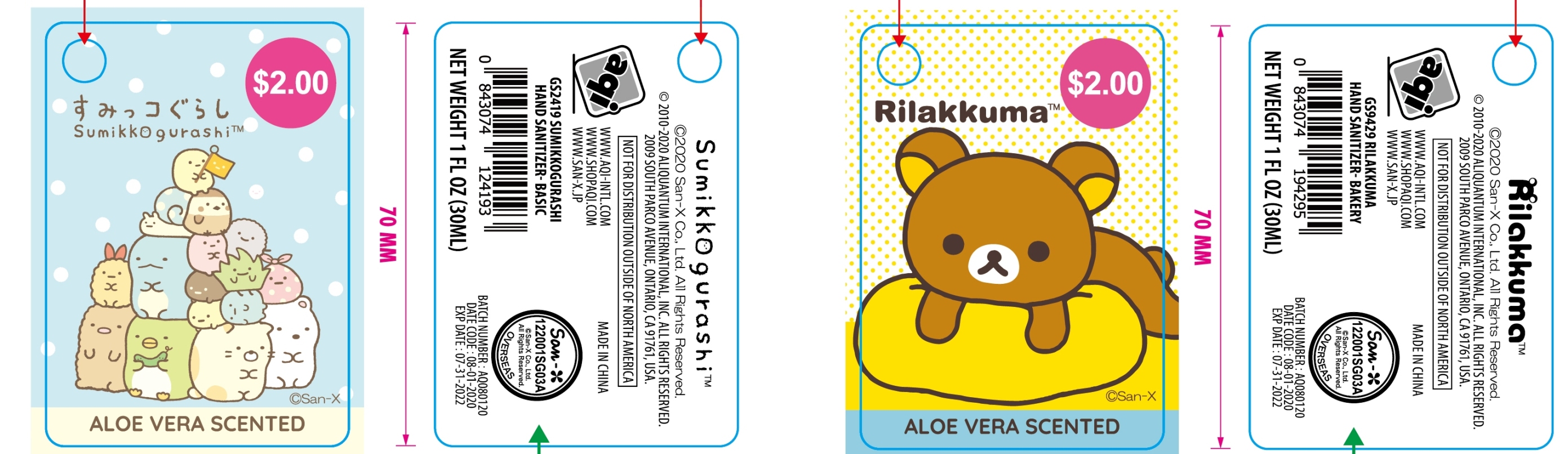 DRUG LABEL: Rilakkuma Aloe Vera Scented
NDC: 75112-009 | Form: SOLUTION
Manufacturer: Zhejiang Shenying Technology Co., Ltd. Jiaojiang Branch
Category: otc | Type: HUMAN OTC DRUG LABEL
Date: 20220915

ACTIVE INGREDIENTS: ALCOHOL 75 mL/100 mL
INACTIVE INGREDIENTS: WATER; CARBOMER 934; TROLAMINE; GLYCEROL FORMAL; ALOE

75112-009 Rilakkuma

Active Ingredient(s)

Ethyl Alcohol 75% v/v

Purpose

Antibacterial

Use

To decrease bacterial on hands

Warnings

For external use only. Flammable. Keep away from heat or flame.

When using this product, avoid contact with eyes. If contact occurs, rinse thoroughly with water.

Stop use and ask a doctor if irritation occurs and redness develops or increases.

Keep out of reach of children. If swallowed, get medical help or contact a Poison Control Center right away.

Directions

Rub a dime sized amount into hands

Inactive ingredients

Water, carbomer, triethanolamine, glycerol, aloe extract